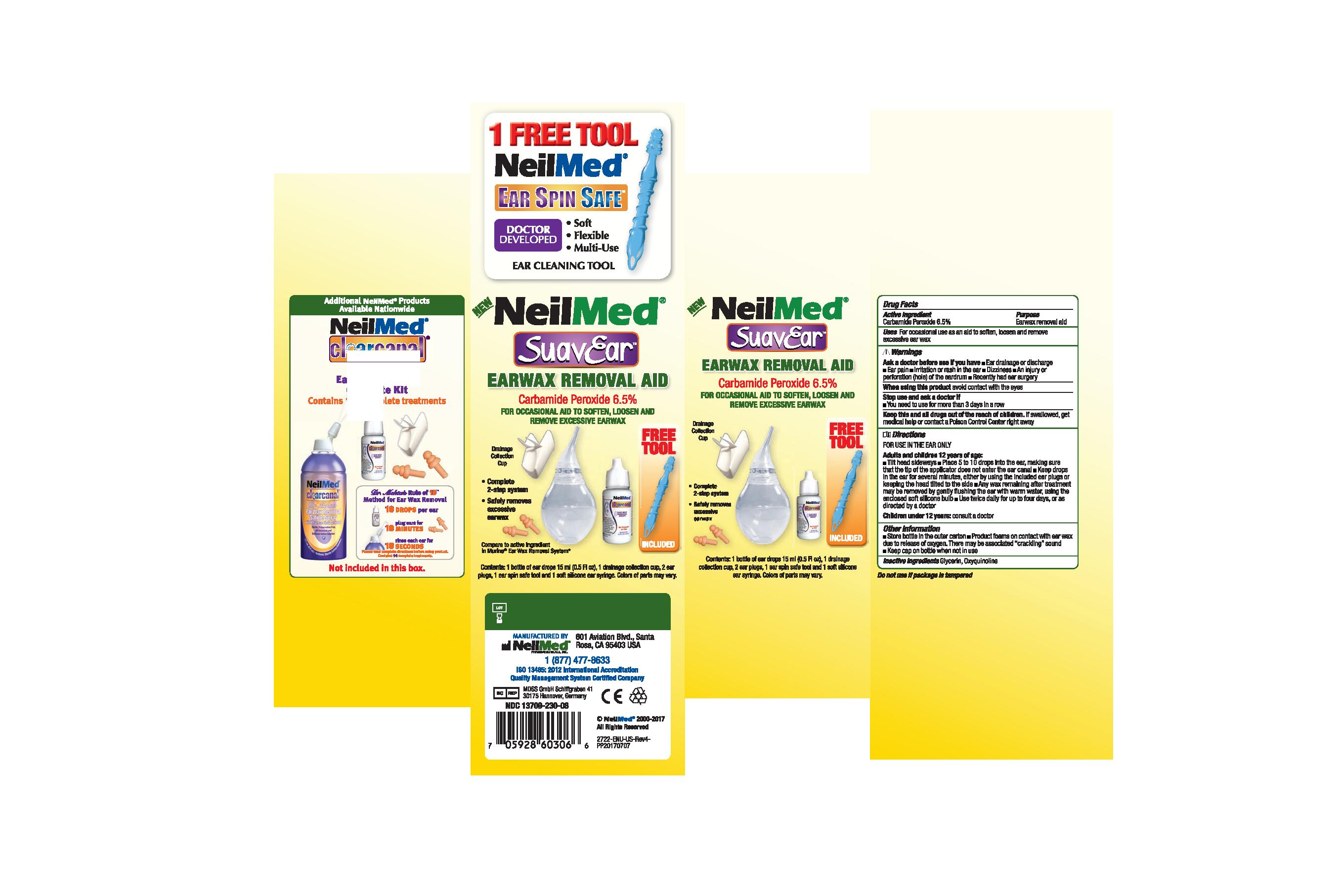 DRUG LABEL: SuavEar Earwax Removal Aid
NDC: 13709-312 | Form: SOLUTION/ DROPS
Manufacturer: NEILMED PHARMACEUTICALS INC
Category: otc | Type: HUMAN OTC DRUG LABEL
Date: 20240111

ACTIVE INGREDIENTS: CARBAMIDE PEROXIDE 65 mg/1 mL
INACTIVE INGREDIENTS: GLYCERIN; OXYQUINOLINE

New Neilmed SuavEar Earwax Removal Aid

Active Ingredient

Carbamide Peroxide 6.5%

Purpose

Earwax Removal Aid

Uses

For occasional use as an aid to soften, loosen and remove excessive earwax

Warnings

Ask a doctor before use if you have

- Ear drainage or discharge
- Ear Pain
- Irritation or rash in the ear
- Dizziness
- An injury or perforation (hole) of the eardrum
- Recently had ear surgery

When using this product

Avoid contact with the eyes

Stop use and ask a doctor if

- You need to use for more than 3 days in a row

Keep this and all drugs out of the reach of children

If swallowed, get medical help or contact a Poison Control Center right away

Directions

FOR USE IN THE EAR ONLY

Adults and children 12 years of age:

- Tilt head sideways
- Place 5 to 10 drops into the ear, making sure that the tip of the applicator does not enter the earcanal
- Keep drops in the ear for sevaral minutes, either by using teh included earplugs or keeping the head tilted to the side
- Any wax remaining after treatment may be removed by gently flushing the ear with warm water, using the enclosed soft silicone bulb
- Use twice daily for upto four days, or as directed by a doctor

Children under 12 years: consult a doctor

Other Information

- Store bottle in the outer carton
- Product foams on contact with earwax due to release of oxygen. There may be associated "crackling" sound.
- Keep cap on bottle when not in use

Inactive Ingredients

Glycerin

Oxyquinoline